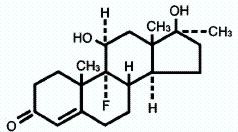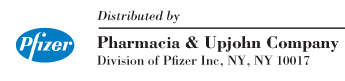 DRUG LABEL: Unknown
Manufacturer: Pharmacia and Upjohn Company
Category: prescription | Type: HUMAN PRESCRIPTION DRUG LABELING
Date: 20060206
DEA Schedule: CIII

Halotestin® CIII
fluoxymesterone
tablets, USP

DESCRIPTION

HALOTESTIN Tablets contain fluoxymesterone, an androgenic hormone.

Fluoxymesterone is a white or nearly white, odorless, crystalline powder, melting at or about 240° C, with some decomposition. It is practically insoluble in water, sparingly soluble in alcohol, and slightly soluble in chloroform.

The chemical name for fluoxymesterone is androst-4-en-3-one, 9-fluoro-11,17-dihydroxy-17-methyl-, (11β,17β)-. The molecular formula is C20H29FO3 and the molecular weight 336.45.

The structural formula is represented below:

Each HALOTESTIN tablet, for oral administration, contains 2 mg, 5 mg or 10 mg fluoxymesterone. Inactive ingredients: calcium stearate, corn starch, FD&C Yellow No. 5, lactose, sorbic acid, sucrose, tragacanth. In addition, the 2 mg tablet contains FD&C Yellow No. 6 and the 5 mg and 10 mg contain FD&C Blue No. 2.

CLINICAL PHARMACOLOGY

Endogenous androgens are responsible for normal growth and development of the male sex organs and for maintenance of secondary sex characteristics. These effects include growth and maturation of the prostate, seminal vesicles, penis, and scrotum; development of male hair distribution, such as beard, pubic, chest, and axillary hair; laryngeal enlargement, vocal cord thickening, and alterations in body musculature and fat distribution. Drugs in this class also cause retention of nitrogen, sodium, potassium, and phosphorus, and decreased urinary excretion of calcium. Androgens have been reported to increase protein anabolism and decrease protein catabolism. Nitrogen balance is improved only when there is sufficient intake of calories and protein.

Androgens are responsible for the growth spurt of adolescence and for eventual termination of linear growth, brought about by fusion of the epiphyseal growth centers. In children, exogenous androgens accelerate linear growth rates, but may cause disproportionate advancement in bone maturation. Use over long periods may result in fusion of the epiphyseal growth centers and termination of the growth process. Androgens have been reported to stimulate production of red blood cells by enhancing production of erythropoietic stimulation factor.

During exogenous administration of androgens, endogenous testosterone release is inhibited through feedback inhibition of pituitary luteinizing hormone (LH). At large doses of exogenous androgens, spermatogenesis may also be suppressed through feedback inhibition of pituitary follicle stimulating hormone (FSH).

Inactivation of testosterone occurs primarily in the liver.

The half-life of fluoxymesterone after oral administration is approximately 9.2 hours.

INDICATIONS AND USAGE

In the male—HALOTESTIN Tablets are indicated for

1. Replacement therapy in conditions associated with symptoms of deficiency or absence of endogenous testosterone.
  1. Primary hypogonadism (congenital or acquired) testicular failure due to cryptorchidism, bilateral torsion, orchitis , vanishing testis syndrome; or orchidectomy.
  2. Hypogonadotropic hypogonadism (congenital or acquired)—idiopathic gonadotropin or LHRH deficiency, or pituitary-hypothalamic injury from tumors, trauma, or radiation.
2. Delayed puberty, provided it has been definitely established as such, and is not just a familial trait.

In the female—HALOTESTIN Tablets are indicated for palliation of androgen-responsive recurrent mammary cancer in women who are more than one year but less than five years postmenopausal, or who have been proven to have a hormone- dependent tumor as shown by previous beneficial response to castration.

CONTRAINDICATIONS

1. Known hypersensitivity to the drug
2. Males with carcinoma of the breast
3. Males with known or suspected carcinoma of the prostate gland
4. Women known or suspected to be pregnant
5. Patients with serious cardiac, hepatic or renal disease

WARNINGS

Hypercalcemia may occur in immobilized patients and in patients with breast cancer. If this occurs, the drug should be discontinued.

Prolonged use of high doses of androgens (principally the 17-α alkyl-androgens) has been associated with development of hepatic adenomas, hepatocellular carcinoma, and peliosis hepatis—all potentially life-threatening complications.

Cholestatic hepatitis and jaundice may occur with 17-α-alkyl-androgens. Should this occur, the drug should be discontinued. This is reversible with discontinuation of the drug.

Geriatric patients treated with androgens may be at an increased risk of developing prostatic hypertrophy and prostatic carcinoma although conclusive evidence to support this concept is lacking.

Edema, with or without congestive heart failure, may be a serious complication in patients with pre-existing cardiac, renal or hepatic disease.

Gynecomastia may develop and occasionally persists in patients being treated for hypogonadism.

Androgen therapy should be used cautiously in males with delayed puberty. Androgens can accelerate bone maturation without producing compensatory gain in linear growth. The effect on bone maturation should be monitored by assessing bone age of the wrist and hand every six months.

This drug has not been shown to be safe and effective for the enhancement of athletic performance. Because of the potential risk of serious adverse health effects, this drug should not be used for such purpose.

PRECAUTIONS

General

Women should be observed for signs of virilization which is usual following androgen use at high doses. Discontinuation of drug therapy at the time of evidence of mild virilism is necessary to prevent irreversible virilization. A decision may be made by the patient and the physician that some virilization will be tolerated during treatment for breast carcinoma.

Patients with benign prostatic hypertrophy may develop acute urethral obstruction. Priapism or excessive sexual stimulation may develop. Oligospermia may occur after prolonged administration or excessive dosage. If any of these effects appear, the androgen should be stopped and if restarted, a lower dosage should be utilized.

This product contains FD&C Yellow No. 5 (tartrazine) which may cause allergic-type reactions (including bronchial asthma) in certain susceptible individuals. Although the overall incidence of FD&C Yellow No. 5 (tartrazine) sensitivity in the general population is low, it is frequently seen in patients who also have aspirin hypersensitivity.

Information for patients

Patients should be instructed to report any of the following: nausea, vomiting, changes in skin color, and ankle swelling. Males should be instructed to report too frequent or persistent erections of the penis and females any hoarseness, acne, changes in menstrual periods or increase in facial hair.

Laboratory tests

Women with disseminated breast carcinoma should have frequent determination of urine and serum calcium levels during the course of androgen therapy (See WARNINGS).

Because of the hepatotoxicity associated with the use of 17-alpha-alkylated androgens, liver function tests should be obtained periodically.

Periodic (every six months) X-ray examinations of bone age should be made during treatment of prepubertal males to determine the rate of bone maturation and the effects of androgen therapy on the epiphyseal centers.

Hemoglobin and hematocrit levels (to detect polycythemia) should be checked periodically in patients receiving long-term androgen administration.

Serum cholesterol may increase during androgen therapy.

Drug interactions

Androgens may increase sensitivity to oral anticoagulants. Dosage of the anticoagulant may require reduction in order to maintain satisfactory therapeutic hypoprothrombinemia.

Concurrent administration of oxyphenbutazone and androgens may result in elevated serum levels of oxyphenbutazone.

In diabetic patients, the metabolic effects of androgens may decrease blood glucose and, therefore, insulin requirements.

Drug/Laboratory test interferences

Androgens may decrease levels of thyroxine-binding globulin, resulting in decreased total T4 serum levels and increased resin uptake of T3 and T4. Free thyroid hormone levels remain unchanged, however, and there is no clinical evidence of thyroid dysfunction.

Carcinogenesis, mutagenesis, impairment Of Fertility

Animal data: Testosterone has been tested by subcutaneous injection and implantation in mice and rats. The implant induced cervical-uterine tumors in mice, which metastasized in some cases. There is suggestive evidence that injection of testosterone into some strains of female mice increases their susceptibility to hepatoma. Testosterone is also known to increase the number of tumors and decrease the degree of differentiation of chemically-induced carcinomas of the liver in rats.

Human data: There are rare reports of hepatocellular carcinoma in patients receiving long-term therapy with androgens in high doses. Withdrawal of the drugs did not lead to regression of the tumors in all cases.

Geriatric patients treated with androgens may be at an increased risk of developing prostatic hypertrophy and prostatic carcinoma although conclusive evidence to support this concept is lacking.

This compound has not been tested for mutagenic potential. However, as noted above, carcinogenic effects have been attributed to treatment with androgenic hormones. The potential carcinogenic effects likely occur through a hormonal mechanism rather than by a direct chemical interaction mechanism.

Impairment of fertility was not tested directly in animal species. However, as noted below under Adverse Reactions, oligospermia in males and amenorrhea in females are potential adverse effects of treatment with HALOTESTIN Tablets. Therefore, impairment of fertility is a possible outcome of treatment with HALOTESTIN.

Pregnancy

Teratogenic effects

Pregnancy Category X. (See CONTRAINDICATIONS.)

Nursing mothers

HALOTESTIN is not recommended for use in nursing mothers.

Pediatric use

Androgen therapy should be used very cautiously in children and only by specialists aware of the adverse effects on bone maturation. Skeletal maturation must be monitored every six months by an X-ray of the hand and wrist (See WARNINGS).

ADVERSE REACTIONS

Endocrine and urogenital

Female: the most common side effects of androgen therapy are amenorrhea and other menstrual irregularities; inhibition of gonadotropin secretion; and virilization, including deepening of the voice and clitoral enlargement. The latter usually is not reversible after androgens are discontinued. When administered to a pregnant woman, androgens can cause virilization of external genitalia of the female fetus.

Male: Gynecomastia, and excessive frequency and duration of penile erections. Oligospermia may occur at high dosage.

Skin and appendages

Hirsutism, male pattern of baldness, seborrhea, and acne.

Fluid and electrolyte disturbances

Retention of sodium, chloride, water, potassium, calcium, and inorganic phosphates.

Gastrointestinal

Nausea, cholestatic jaundice, alterations in liver function tests, rarely hepatocellular neoplasms and peliosis hepatis (See WARNINGS).

Hematologic

Suppression of clotting factors II, V, VII, and X, bleeding in patients on concomitant anticoagulant therapy, and polycythemia.

Nervous system

Increased or decreased libido, headache, anxiety, depression, and generalized paresthesia.

Allergic

Hypersensitivity, including skin manifestations and anaphylactoid reactions.

DRUG ABUSE AND DEPENDENCE

Controlled Substance Class

Fluoxymesterone is a controlled substance under the Anabolic Steroids Control Act, and HALOTESTIN Tablets has been assigned to Schedule III.

OVERDOSAGE

There have been no reports of acute overdosage with the androgens.

DOSAGE AND ADMINISTRATION

The dosage will vary depending upon the individual, the condition being treated, and its severity. The total daily oral dose may be administered singly or in divided (three or four) doses.

Male hypogonadism

For complete replacement in the hypogonadal male, a daily dose of 5 to 20 mg will suffice in the majority of patients. It is usually preferable to begin treatment with full therapeutic doses which are later adjusted to individual requirements. Priapism is indicative of excessive dosage and is indication fortemporary withdrawal of the drug.

Delayed puberty

Dosage should be carefully titrated utilizing a low dose, appropriate skeletal monitoring, and by limiting the duration of therapy to four to six months.

Inoperable carcinoma of the breast in the female

The recommended total daily dose for palliative therapy in advanced inoperable carcinoma of the breast is 10 to 40 mg. Because of its short action, fluoxymesterone should be administered to patients in divided, rather than single, daily doses to ensure more stable blood levels. In general, it appears necessary to continue therapy for at least one month for a satisfactory subjective response, and for two to three months for an objective response.

HOW SUPPLIED

HALOTESTIN Tablets, round and scored, are available in the following strengths and colors:

2 mg (peach)
Bottles of 100 NDC 0009-0014-01

5 mg (light green)
Bottles of 100 NDC 0009-0019-06

10 mg (green)
Bottles of 30 NDC 0009-0036-03
Bottles of 100 NDC 0009-0036-04

Store at controlled room temperature 20° to 25°C (68° to 77°F) [see USP].

Rx only

810 804 708

692851

May 2002